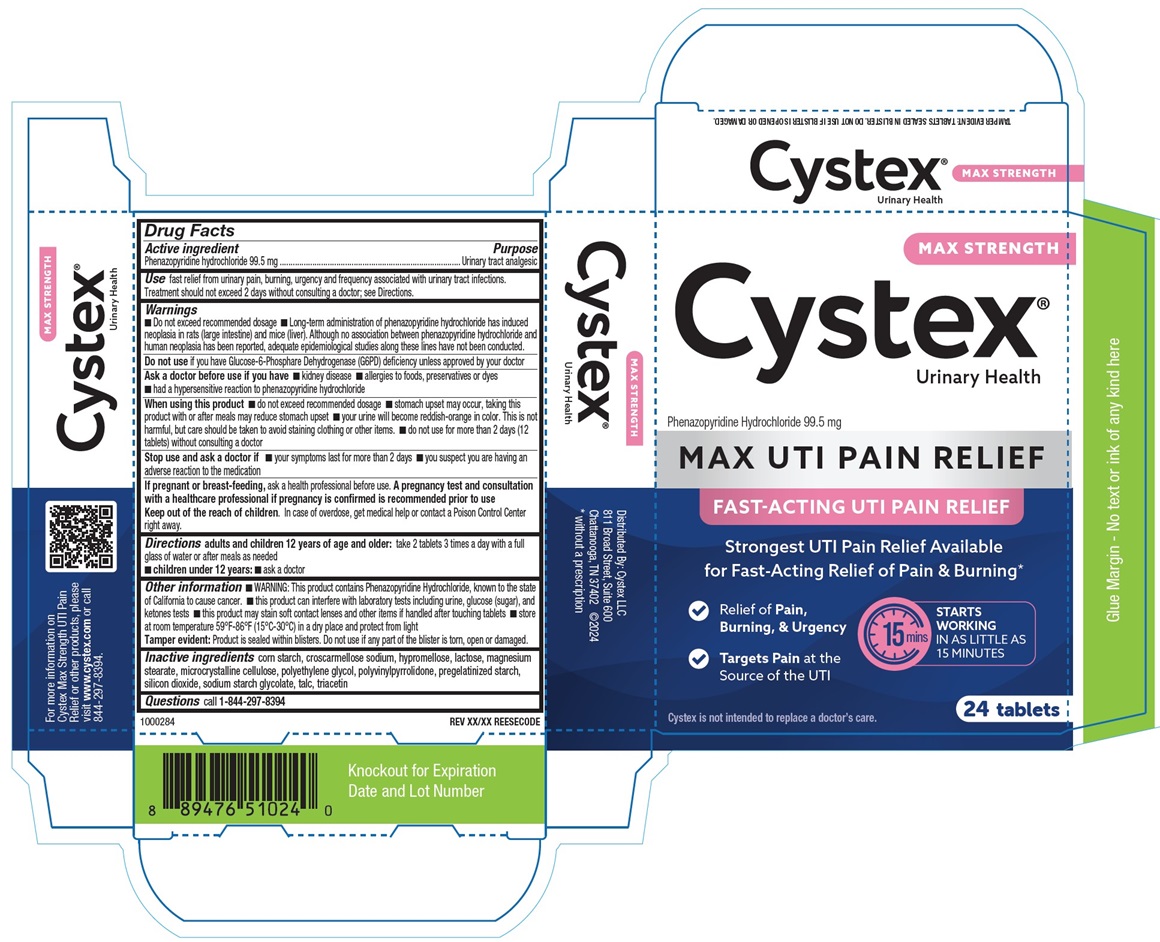 DRUG LABEL: Cystex Max UTI Pain Relief
NDC: 69693-514 | Form: TABLET
Manufacturer: Clarion Brands, LLC
Category: otc | Type: HUMAN OTC DRUG LABEL
Date: 20260114

ACTIVE INGREDIENTS: PHENAZOPYRIDINE HYDROCHLORIDE 99.5 mg/1 1
INACTIVE INGREDIENTS: STARCH, CORN; CROSCARMELLOSE SODIUM; HYPROMELLOSE, UNSPECIFIED; LACTOSE, UNSPECIFIED FORM; MAGNESIUM STEARATE; MICROCRYSTALLINE CELLULOSE; POLYETHYLENE GLYCOL, UNSPECIFIED; POVIDONE, UNSPECIFIED; SILICON DIOXIDE; SODIUM STARCH GLYCOLATE TYPE A; TALC; TRIACETIN

Drug Facts

Active ingredient

Phenazopyridine hydrochloride 99.5 mg

Purpose

Urinary tract analgesic

INDICATIONS AND USAGE

Use fast relief from urinary pain, burning, urgency and frequency associated with urinary tract infections. Treatment should not exceed 2 days without consulting a doctor; see Directions.

Warnings

- Do not exceed recommended dosage
- Long-term administration of phenazopyridine hydrochloride has induced neoplasia in rats (large intestine) and mice (liver). Although no association between phenazopyridine hydrochloride and human neoplasia has been reported, adequate epidemiological studies along these lines have not been conducted.

Do not use

if you have Glucose-6-Phosphare Dehydrogenase (G6PD) deficiency unless approved by your doctor

Ask a doctor before use if you have

- kidney disease
- allergies to foods, preservatives or dyes
- had a hypersensitive reaction to phenazopyridine hydrochloride

When using this product

- do not exceed recommended dosage
- stomach upset may occur, taking this product with or after meals may reduce stomach upset
- your urine will become reddish-orange in color. This is not harmful, but care should be taken to avoid staining clothing or other items.
- do not use for more than 2 days (12 tablets) without consulting a doctor

Stop use and ask a doctor if

- your symptoms last for more than 2 days
- you suspect you are having an adverse reaction to the medication

PREGNANCY OR BREAST FEEDING

If pregnant or breast-feeding, ask a health professional before use. A pregnancy test and consultation with a healthcare professional if pregnancy is confirmed is recommended prior to use
Keep out of the reach of children. In case of overdose, get medical help or contact a Poison Control Center right away.

Directions

Adults and children 12 years of age and older:take 2 tablets 3 times a day with a full glass of water or after meals as needed

- children under 12 years:
- ask a doctor

Other information

- WARNING: This product contains Phenazopyridine Hydrochloride, known to the state of California to cause cancer.
- this product can interfere with laboratory tests including urine, glucose (sugar), and ketones tests
- this product may stain soft contact lenses and other items if handled after touching tablets
- store at room temperature 59°F-86°F (15°C-30°C) in a dry place and protect from light

Tamper evident:Product is sealed within blisters. Do not use if any part of the blister is torn, open or damaged.

Inactive ingredients

corn starch, croscarmellose sodium, hypromellose, lactose, magnesium stearate, microcrystalline cellulose, polyethylene glycol, polyvinylpyrrolidone, pregelatinized starch, silicon dioxide, sodium starch glycolate, talc, triacetin

Questions

call 1-844-297-8394

PRINCIPAL DISPLAY PANEL

MAX STRENGTH
Cystex®
Urinary Health
Phenazopyridine Hydrochloride 99.5 mg
MAX UTI PAIN RELIEF
FAST-ACTING UTI PAIN RELIEF
Strongest UTI Pain Relief Available
for Fast-Acting Relief of Pain & Burning*
√Relief of Pain, Burning, & Urgency
√ Targets Painat the Source of the UTI
STARTS
WORKING
IN AS LITTLE AS
15 MINUTES
Cystex is not intended to replace a doctor's care.
24 Tablets
TAMPER EVIDENT: TABLETS SEALED IN BLISTER. DO NOT USE IF BLISTER IS OPENED OR DAMAGED.
1000284
REV XX/XX REESECODE
For more information on
Cystex Max Strength UTI Pain
Relief or other products, please
visit www.cystex.comor call
844-297-8394
Distributed by: Cystex LLC
811 Broad Street, Suite 600
Chattanooga, TN 37402 ©2024
*without a prescription